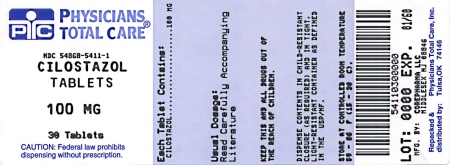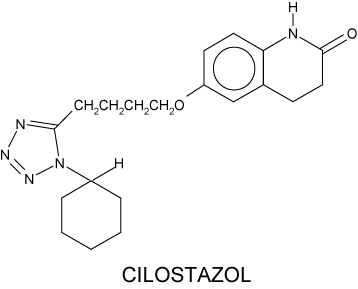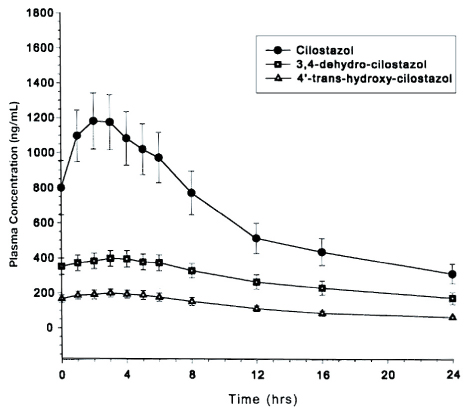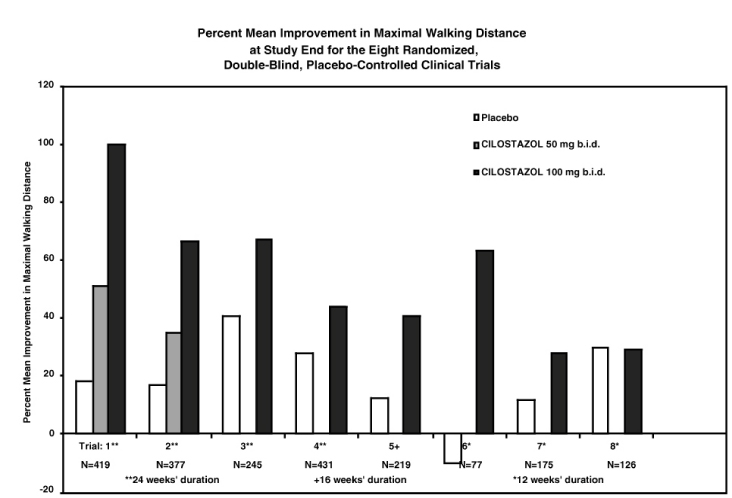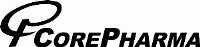 DRUG LABEL: Cilostazol
NDC: 54868-5411 | Form: TABLET
Manufacturer: Physicians Total Care, Inc.
Category: prescription | Type: HUMAN PRESCRIPTION DRUG LABEL
Date: 20101115

ACTIVE INGREDIENTS: CILOSTAZOL 100 mg/1 1
INACTIVE INGREDIENTS: CARBOXYMETHYLCELLULOSE CALCIUM; STARCH, CORN; HYPROMELLOSES; MAGNESIUM STEARATE; CELLULOSE, MICROCRYSTALLINE

Cilostazol Tablets, USP
50 mg and 100 mg
Rx only

CONTRAINDICATION

Cilostazol and several of its metabolites are inhibitors of phosphodiesterase III. Several drugs with this pharmacologic effect have caused decreased survival compared to placebo in patients with class III-IV congestive heart failure. Cilostazol is contraindicated in patients with congestive heart failure of any severity.

DESCRIPTION

Cilostazol is a quinolinone derivative that inhibits cellular phosphodiesterase (more specific for phosphodiesterase III). The empirical formula of cilostazol is C20H27N5O2, and its molecular weight is 369.46. Cilostazol is 6-[4-(1-cyclohexyl-1H-tetrazol-5-yl)butoxy]-3,4-dihydro-2(1H)-quinolinone, CAS-73963-72-1. The structural formula is:

Cilostazol occurs as white to off-white crystals or as a crystalline powder that is slightly soluble in methanol and ethanol, and is practically insoluble in water, 0.1 N HCl, and 0.1 N NaOH.

Cilostazol Tablets, USP for oral administration are available as 50 mg or 100 mg round, white debossed tablets. Each tablet, in addition to the active ingredient, contains the following inactive ingredients: carboxymethylcellulose calcium, corn starch, hypromellose, magnesium stearate and microcrystalline cellulose.

CLINICAL PHARMACOLOGY

Mechanism of Action

The mechanism of the effects of Cilostazol Tablets, USP on the symptoms of intermittent claudication is not fully understood. Cilostazol Tablets, USP and several of its metabolities are cyclic AMP (cAMP) phosphodiesterase III inhibitors (PDE III inhibitors), inhibiting phosphodiesterase activity and suppressing cAMP degration with a resultant increase in cAMP in platelets and blood vessels, leading to inhibition of platelet aggregation and vasodilation, respectively.

Cilostazol Tablets, USP inhibits platelet aggregation induced by a variety of stimuli, including thrombin, ADP, collagen, arachidonic acid, epinephrine, and shear stress. Effects on circulating plasma lipids have been examined in patients taking Cilostazol Tablets, USP. After 12 weeks, as compared to placebo, Cilostazol Tablets, USP 100 mg b.i.d. produced a reduction in triglycerides of 29.3 mg/dL (15%) and an increase in HDL-cholesterol of 4.0 mg/dL (≡ 10%).

Cardiovascular Effects

Cilostazol affects both vascular beds and cardiovascular function. It produces non-homogeneous dilation of vascular beds, with greater dilation in femoral beds than in vertebral, carotid or superior mesenteric arteries. Renal arteries were not responsive to the effects of cilostazol.

In dogs or cynomolgous monkeys, cilostazol increased heart rate, myocardial contractile force, and coronary blood flow as well as ventricular automaticity, as would be expected for a PDE III inhibitor. Left ventricular contractility was increased at doses required to inhibit platelet aggregation. A-V conduction was accelerated. In humans, heart rate increased in a dose-proportional manner by a mean of 5.1 and 7.4 beats per minute in patients treated with 50 and 100 mg b.i.d., respectively. In 264 patients evaluated with Holter monitors, numerically more cilostazol-treated patients had increases in ventricular premature beats and non-sustained ventricular tachycardia events than did placebo-treated; the increases were not dose-related.

Pharmacokinetics

Cilostazol Tablets, USP is absorbed after oral administration. A high fat meal increases absorption, with an approximately 90% increase in Cmax and a 25% increase in AUC. Absolute bioavailability is not known. Cilostazol is extensively metabolized by hepatic cytochrome
P-450 enzymes, mainly 3A4, and, to a lesser extent, 2C19, with metabolites largely excreted in urine. Two metabolites are active, with one metabolite appearing to account for at least 50% of the pharmacologic (PDE III inhibition) activity after administration of Cilostazol Tablets, USP. Pharmacokinetics are approximately dose proportional. Cilostazol and its active metabolites have apparent elimination half-lives of about 11 to 13 hours. Cilostazol and its active metabolites accumulate about 2-fold with chronic administration and reach steady state blood levels within a few days. The pharmacokinetics of cilostazol and its two major active metabolites were similar in healthy normal subjects and patients with intermittent claudication due to peripheral arterial disease (PAD).

The mean ± SEM plasma concentration-time profile at steady state after multiple dosing of Cilostazol Tablets, USP 100 mg b.i.d. is shown below:

Plasma Concentration Time profile

Distribution

Plasma Protein and Erythrocyte Binding:
Cilostazol is 95 to 98% protein bound, predominantly to albumin. The mean percent binding for 3,4-dehydro-cilostazol is 97.4% and for 4'-trans-hydroxy-cilostazol is 66%. Mild hepatic impairment did not affect protein binding. The free fraction of cilostazol was 27% higher in subjects with renal impairment than in normal volunteers. The displacement of cilostazol from plasma proteins by erythromycin, quinidine, warfarin, and omeprazole was not clinically significant.

Metabolism and Excretion:

Cilostazol is elminated predominately by metabolism and subsequent urinary excretion of metabolites. Based on in vitro studies, the primary isoenzymes involved in cilostazol's metabolism are CYP3A4 and, to a lesser extent, CYP2C19. The enzyme responsible for metabolism of 3,4-dehydro-cilostazol, the most active of the metabolites,is unknown.

Following oral administration of 100 mg radiolabeled cilostazol, 56% of the total analytes in plasma was cilostazol, 15% was 3,4-dehydro-cilostazol (4 to 7 times as active as cilostazol), and 4% was 4'-trans-hydroxy-cilostazol (one fifth as active as cilostazol). The primary route of elimination was via the urine (74%), with the remainder excreted in feces (20%). No measurable amount of unchanged cilostazol was excreted in the urine, and less than 2% of the dose was excreted as 3,4-dehydro-cilostazol. About 30% of the dose was excreted in urine as 4'trans-hydroxy-cilostazol. The remainder was excreted asother metabolites, non of which exceeded 5%. There was no evidence of induction of hepatic microenzymes.

Special Populations:

Age and Gender

The total and unbound oral clearances, adjusted for body weight, of cilostazol and its metabolites were not significantly different with respect to age and/or gender across a 50-to-80-year-old age range.

Smokers

Population pharmacokinetic analysis suggests that smoking decreased cilostazol exposure by about 20%.

Hepatic Impairment

The pharmacokinetics of cilostazol and its metabolites were similar with mild hepatic disease as compared to healthy subjects.

Patients with moderate or severe hepatic impairment have not been studied.

Renal Impairment

The total pharmacologic activity of cilostazol and its metabolites was similar in subjects with mild to moderate renal impairment and in normal subjects. Severe renal impairment increases metabolite levels and alters protein bindingof the parent and metabolites. The expected pharmacologic activity, however, based on plasma concentrations and relative PDE III inhibiting potency of patent drug and metabolites, appeared little changed. Patients on dialysis have not been studied, but, it is unlikely that cilostazol can be removed efficiently by dialysis because of its high protein binding (95 to 98%).

Pharmacokinetic and Pharmacodynamic Drug-Drug Interactions:
Cilostazol could have pharmacodynamic interactions with other inhibitors of platelet function and pharmacokinetic interactions because of effects of other drugs on its metabolism by CYP3A4 or CYP2C19. A reduced dose of Cilostazol Tablets, USP should be considered when taken concomitantly with CYP3A4 or CYP2C19 inhibitors. Cilostazol does not appear to inhibit CYP3A4 (see Pharmacokinetic and Pharmacodynamic Drug-Drug Interactions, Lovastatin).

Aspirin

Short-term (≤4 days) coadministration of aspirin with Cilostazol Tablets, USP increased the inhibition of arachidonic acid-induced ex vivoplatelet aggregation by 20% compared to Cilostazol Tablets, USP alone and by 48% compared to aspirin alone. However, short-term coadministration of aspirin with Cilostazol Tablets, USP had no clinically significant impact on PT, aPTT, or bleeding time compared to aspirin alone. Effects of long-term coadministration in the general population are unknown. In eight randomized, placebo-controlled, double-blind clinical trials, aspirin was coadministered with cilostazol to 201 patients. The most frequent doses and mean durations of aspirin therapy wer 75 to 81 mg daily for 137 days (107 patients) and 325 mg daily for 54 days (85 patients). There was no apparent increases in incidence of hemorrhagic adverse effects in patients taking cilostazol and aspirin compared to patients taking placebo and equivalent doses of aspirin.

Warfarin

The cytochrome P-450 isoenzymes involved in the metabolism of R-warfarin are CYP3A4, CYP1A2, and CYP2C19, and in the metabolism of S-warfarin, CYP2C9. Cilostazol did not inhibit either the metabolism or the pharmacologic effects (PT, aPTT, bleeding time, or platelet aggregation) of R- and S-warfarin after a single 25-mg dose of warfarin. The effecr of concomitant multiple dosing of warfarin and Cilostozol Tablets, USP on the pharmacokinetics and pharmacodynamics of both drugs is unknown.

Clopidogrel

Mulitiple doses of clopidogrel do not significantly increase steadystate plasma concentrations of cilostzol.

INHIBITORS OF CYP3A4

Strong Inhibitors of CYP3A4:
A priming dose of ketoconazole 400 mg (a strong inhibitor of CYP3A4), was given one day prior to coadminstration of single doses of ketoconazole 400 mg and cilostazol 100 mg. This regimen increased cilostazol Cmax by 94% and AUC by 117%. Other strong inhibitors of CYP3A4, such as intraconazole, fluconazole, miconazole, fluvoxamine, fluoxetine, nefazodone, and sertraline, would be expected to have a similar effect (see DOSAGE AND ADMINISTRATION).

Moderate Inhibitors of CYP3A4:
1. Erythromycin and other macrolide antibiotics: Erythromycin is a moderately strong inhibitor of CYP3A4. Coadministration of erythromycin 500 mg q 8h with a single dose of cilostazol 100 mg increased cilostazol Cmax by 47% and AUC by 73%. Inhibition of cilostazol metabolism by erythromycin increased the AUC of 4'-trans-hydroxy-cilostazol by 141%. Other macrolide antibiotics (e.g., clarithromycin), but not all (e.g. azithromycin), would be expected to have a similar efect (see DOSAGE AND ADMINISTRATION).
2. Diltiazem: Diltiazem 180 mg decreased the clearance of cilostazol by ~30% and AUC increased ~40% (see DOSAGE AND ADMINITRATION).
3. Grapefruit Juice: Grapefruit juice increased the Cmax of cilostazol by ~50%, but had not effect on AUC.

INHIBITORS OF CYP2C19

Omeprazole: Coadministration of omeprazole did not significantly affect the metabolism of cilostazol, but the systemic exposure to 3,4-dehydro-cilostazol was increased by 69%, probably the result of omeprazole's potent inhibition of CYP2C19 (see DOSAGE AND ADMINISTRATION).

Quinidine

Concomitant administration of quinidine with a single dose of cilostazol 100 mg did not alter cilostazol pharmacokinetics.

Lovastatin

The concomitant administration of lovastatin with cilostazol decreases cilostazol Css, max and AUC, by 15%. There is also a decrease, although nonsignificant, in cilostazole metaboite concentrations. Coadministration of cilostazole with lovastatin increased lovastatin and β-hydroxi lovastatin AUC approximately 70%. This is most likely clinically insignificant.

CLINICAL STUDIES:

The ability of Cilostazol Tablets, USP to improve walking distance in patients with stable intermittent claudication was studied in eight large, randomized, placebo-controlled, double-blind trials of 12 to 24 weeks’ duration using dosages of 50 mg b.i.d. (n=303), 100 mg b.i.d. (n=998), and placebo (n=973). Efficacy was determined primarily by the change in maximal walking distance from baseline (compared to change on placebo) on one of several standardized exercise treadmill tests.

Compared to patients treated with placebo, patients treated with Cilostazol Tablets, USP 50 or 100 mg b.i.d. experienced statistically significant improvements in walking distances both for the distance before the onset of claudication pain and the distance before exercise-limiting symptoms supervened (maximal walking distance). The effect of Cilostazol Tablets, USP on walking distance was seen as early as the first on-therapy observation point of two or four weeks.

The following figure depicts the percent mean improvement in maximal walking distance at study end for each of the eight studies.

Percent Mean Improvement in Maximal Walking Distance at Study End for the Eight Randomized, Double-Blind, Placebo-Controlled Clinical Trials

Across the eight clinical trials, the range of improvement in maximal walking distance in patients treated with Cilostazol Tablets, USP
100 mg b.i.d., expressed as the percent mean change from baseline, was 28% to 100%.

The corresponding changes in the placebo group were –10% to 41%.

The Walking Impairment Questionnaire, which was administered in six of the eight clinical trials, assesses the impact of a therapeutic intervention on walking ability. In a pooled analysis of the six trials, patients treated with either Cilostazol Tablets, USP 100 mg b.i.d. or 50 mg b.i.d. reported improvements in their walking speed and walking distance as compared to placebo. Improvements in walking performance were seen in the various subpopulations evaluated, including those defined by gender, smoking status, diabetes mellitus, duration of peripheral artery disease, age, and concomitant use of beta blockers or of calcium channel blockers. Cilostazol Tablets, USP has not been studied in patients with rapidly progressing claudication or in patients with leg pain at rest, ischemic leg ulcers, or gangrene. Its long-term effects on limb preservation and hospitalization have not been evaluated.

A randomized, double-blind, placebo-controlled Phase IV study was conducted to assess the long-term effects of cilostazol, with respect to mortality and safety, in 1,439 patients with the intermittent claudication and no heart failure. The trial stopped early due to enrollment difficulties and a lower than expected overall death rate. With respect to mortality, the observed 36-month Kaplan-Meier event rate for deaths on study drug with a median time of 18 months was 5.6% (95% CI of 2.8 to 8.4%) on cilostazol and 6.8%(95% CI of 1.9 to 11.5%) on placebo. These data appear to be sufficient to exclude a 75% increase in the risk of mortality on cilostazol, which s the a priori study hypothesis.

INDICATIONS AND USAGE

Cilostazol Tablets, USP are indicated for the reduction of symptoms of intermittent claudication, as indicated by an increased walking distance.

CONTRAINDICATIONS

Cilostazol and several of its metabolites are inhibitors of phosphodiesterase III. Several drugs with this pharmacologic effect have caused decreased survival compared to placebo in patients with class III-IV congestive heart failure. Cilostazol Tablets, USP are contraindicated in patients with congestive heart failure of any severity.

Cilostazol Tablets, USP are contraindicated in patients with haemostatic disorders or active pathologic bleeding, such as bleeding peptic ulcer and intracranial bleeding. Cilostazol Tablets, USP inhibit platelet aggregation in a reversible manner.

Cilostazol Tablets, USP are contraindicated in patients with known or suspected hypersensitivity to any of its components.

PRECAUTIONS

Hematologic Adverse Reactions

Rare cases have been reported of thrombocytopenia or leucopenia progressing to agranulocytosis when cilostazol was not immediately discontinued. The agranulocytosis, however, was reversible on discontinuation of Cilostazol.

Use with Clopidogrel

There is limited information with respect to the efficacy or safety of the concurrent use of cilostazol and clopidogrel, a platelet-aggregation inhibiting drug indicated for use in patients with peripheral arterial disease. Although it cannot be determined whether there was an additive effect on bleeding times during concomitant administration with cilostazol and clopidogrel, caution is advised for checking bleeding times during coadministration.

Information for Patients

Please refer to the patient package insert.
Patients should be advised:

- to read the patient package insert for Cilostazol Tablets USPcarefully before starting therapy and to reread it each time therapy is renewed in case the information has changed.
- to take cilostazol at least one-half hour before or two hours after food.
- that the beneficial effects of cilostazol on the symptoms of intermittent claudication may not be immediate. Although the patient may experience benefit in 2 to 4 weeks after initiation of therapy, treatment for up to 12 weeks may be required before a beneficial effect is experienced.

Hepatic Impairment

Patients with moderate or severe hepatic impairment have not been studied in clinical trials.

Special caution is advised when Cilostazol Tablets, USP is used in such patients.

Renal Impairment

Patients on dialysis have not been studied, but, it is unlikely that cilostazol can be removed efficiently by dialysis because of its high protein binding (95 to 98%).

Special caution is advised when Cilostazol Tablets, USP is used in patients with severe renal impairment; estimated creatinine clearence, <25 ml/min.

Drug Interactions

Since Cilostazol Tablets, USP is extensively metabolized by cytochrome P-450 isoenzymes, caution should be exercised when Cilostazol Tablets, USP is coadministered with inhibitors of CYP3A4 such as ketoconazole and erythromycin or inhibitors of CYP2C19 such as omeprazole. Pharmacokinetic studies have demonstrated that omeprazole and erythromycin significantly increased the systemic exposure of cilostazol and/or its major metabolites. Population pharmacokinetic studies showed higher concentrations of cilostazol among patients concurrently treated with diltiazem, an inhibitor of CYP3A4 (see CLINICAL PHARMACOLOGY, Pharmacokinetic and Pharmacodynamic Drug-Drug Interactions). Cilostazol Tablets, USP does not, however, appear to cause increased blood levels of drugs metabolized by CYP3A4, as it had no effect on lovastatin, a drug with metabolism very sensitive to CYP3A4 inhibition.

Use with other antiplatelet agents

Cilostazol Tablets, USP inhibits platelet aggregation but in a reversible manner. Cuation is advised in patients at risk of bleeding from surgery or pathologic processes. Platelet aggregability returns to normal within 96 hours of stopping Cilostazole Tablets, USP. Cuation is advised in patients receiving both Cilostazol Tablets, USP and any other antiplatelet agent, or in patients with thrombocytopenia.

Cardiovascular Toxicity

Repeated oral administration of cilostazol to dogs (30 or more mg/kg/day for 52 weeks, 150 or more mg/kg/day for 13 weeks, and 450 mg/kg/day for 2 weeks), produced cardiovascular lesions that included endocardial haemorrhage, hemosiderin deposition and fibrosis inthe left ventricle, haemorrhage in the right atrial wall, haemorrhage and necrosis of the smooth muscle in the wall of the coronary artery, intimal thickening of the coronary artery, and coronary arteritis and periarteritis. At the lowest dose associated with cardiovascular lesions in the 52-week study, systemic exposure (AUC) tounbound cilostazol was less than that seen in humans at the maximum recommended human dose (MRHD) of 100 mg b.i.d. Similar lesions have been reported in dogs following the administration of other positive inotropic agents (including PDE III inhibitors) and/or vasodilating agents. No cardiovascular lesions were seen in rats following 5 or 13 weeks of administration of cilostazol at doses up to 1500 mg/kg/day. At this dose, systemic exposures (AUCs) to unbound cilostazol were only about 1.5 and 5 times (male and female rats, respectively) the exposure seen in humans at the MRHD. Cardiovascular lesionswere also not seen in rats following 52 weeks of administration of cilostazol at doses up to 150 mg/kg/day. At this dose, systemic exposure (AUCs) tounbound cilostazol were about 0.5 and 5 times (male and female rates, respectively) the exposure in humans at the MRHD. In female rats, cilostazol AUCs were similar at 150 and 1500 mg/kg/day. Cardiovascular lesions were also not observed in monkeys after oral administration of cilostazol for 13 weeks at doses up to 1800 mg/kg/day. While this dose of cilostazol produced pharmacologic effects in monkeys, plasma cilostazol levels were less than those seen in humans given the MRHD, and those seen in dogs given doses associated with cardiovascular lesions.

Carcinogenesis, Mutagenesis, Impairment of Fertility

Dietary administration of cilostazol to male and female rats and mice for up to 104 weeks, at doses up to 500 mg/kg/day in rats and 1000 mg/kg/day in mice, revealed no evidence of carcinogenic potential. The maximum doses administered in both rat and mouse studies were, on a systemic exposure basis, less than the human exposure at the MRHD of the drug. Cilostazol tested negative in bacterial gene mutation, bacterial DNA repair, mammalian cell gene mutation, and mouse in vivo bone marrow chromosomal aberration assays. It was, however, associated with a significant increase in chromosomal aberrations in the in vitro Chinese Hamster Ovary Cell assay.

Cilostazol did not affect fertility or mating performance of male and female rats at doses as high as 1000 mg/kg/day. At this dose, systemic exposures (AUCs) to unbound cilostazol were less than 1.5 times in males, and about 5 times in females, the exposure in humans at the MRHD.

Pregnancy

Pregnancy Category C: In a rat developmental toxicity study, oral administration of 1000 mg cilostazol/kg/day was associated with decreased fetal weights, and increased incidences of cardiovascular, renal, and skeletal anomalies (ventricular septal, aortic arch, and subclavian artery abnormalities, renal pelvic dilation, 14th rib, and retarded ossification). At this dose, systemic exposure to unbound cilostazol in nonpregnant rats was about 5 times the exposure in humans given the MRHD. Increased incidences of ventricular septal defect and retarded ossification were also noted at 150 mg/kg/day (5 times the MRHD on a systemic exposure basis). In a rabbit developmental toxicity study, an increased incidence of retardation of ossification of the sternum was seen at doses as low as 150 mg/kg/day. In nonpregnant rabbits given 150 mg/kg/day, exposure to unbound cilostazol was considerably lower than that seen in humans given the MRHD, and exposure to 3,4-dehydro-cilostazol was barely detectable.

When cilostazol was administered to rats during late pregnancy and lactation, an increased incidence of stillborn and decreased birth weights of offspring was seen at doses of 150 mg/kg/day (5 times the MRHD on a systemic exposure basis).

There are no adequate and well-controlled studies in pregnant women.

Nursing Mothers

Transfer of cilostazol into milk has been reported in experimental animals (rats). Because of the potential risk to nursing infants, a decision should be made to discontinue nursing or to discontinue cilostazol

Pediatric Use

The safety and effectiveness of cilostazol in pediatric patients have not been established.

Geriatric Use

Of the total number of subjects (n = 2274) in clinical studies of cilostazol, 56 percent were 65-years-old and over, while 16 percent were 75-years-old and over. No overall differences in safety or effectiveness were observed between these subjects and younger subjects, and other reported clinical experience has not identified differences in responses between the elderly and younger patients, but greater sensitivity of some older individuals cannot be ruled out. Pharmacokinetic studies have not disclosed any age-related effects on the absorption, distribution, metabolism, and elimination of cilostazol and its metabolites.

ADVERSE REACTIONS

Adverse events were assessed in eight placebo-controlled clinical trials involving 2274 patients exposed to either 50 or 100 mg b.i.d. cilostazol tablets (n=1301) or placebo (n=973), with a median treatment duration of 127 days for patients on cilostazol and 134 days for patients on placebo.

The only adverse event resulting in discontinuation of therapy in ≥ 3% of patients treated with cilostazol 50 or 100 mg b.i.d. was headache, which occurred with an incidence of 1.3%, 3.5%, and 0.3% in patients treated with cilostazol 50 mg b.i.d., 100 mg b.i.d. or placebo, respectively. Other frequent causes of discontinuation included palpitation and diarrhea, both 1.1% for cilostazol (all doses) versus 0.1% for placebo.

The most commonly reported adverse events, occurring in ≥ 2% of patients treated with cilostazol 50 or 100 mg b.i.d., are shown in the table below.

Other events seen with an incidence of ≥ 2%, but occurring in the placebo group at least as frequently as in the 100 mg b.i.d. group were: asthenia, hypertension, vomiting, leg cramps, hyperesthesia, paresthesia, dyspnea, rash, hematuria, urinary tract infection, flu syndrome, angina pectoris, arthritis, and bronchitis.

Most Commonly Reported AEs (Incidence ≥2%) in Patients on Cilostazol 50 mg b.i.d. or 100 mg
b.i.d. and Occurring at a Rate in the 100 mg b.i.d.
Group Higher Than in Patients on Placebo
Adverse Events (AEs) by Body System | Cilostazol 50 mg b.i.d. (N=303) % | Cilostazol 100 mg b.i.d. (N=998) % | Placebo (N=973) %
BODY AS A WHOLE
Abdominal pain | 4 | 5 | 3
Back pain | 6 | 7 | 6
Headache | 27 | 34 | 14
Infection | 14 | 10 | 8
CARDIOVASCULAR
Palpitation | 5 | 10 | 1
Tachycardia | 4 | 4 | 1
DIGESTIVE
Abnormal stools | 12 | 15 | 4
Diarrhea | 12 | 19 | 7
Dyspepsia | 6 | 6 | 4
Flatulence | 2 | 3 | 2
Nausea | 6 | 7 | 6
METABOLIC & NUTRITIONAL
Peripheral edema | 9 | 7 | 4
MUSCULO-SKELETAL
Myalgia | 2 | 3 | 2
NERVOUS
Dizziness | 9 | 10 | 6
Vertigo | 3 | 1 | 1
RESPIRATORY
Cough increased | 3 | 4 | 3
Pharyngitis | 7 | 10 | 7
Rhinitis | 12 | 7 | 5

Less frequent adverse events (< 2%) that were experienced by patients exposed to cilostazol 50 mg b.i.d. or 100 mg b.i.d. in the eight controlled clinical trials and that occurred at a frequency in the 100 mg b.i.d. group greater than in the placebo group, regardless of suspected drug relationship, are listed below.

Body As a Whole: Chills, face edema, fever, generalized edema, malaise, neck rigidity, pelvic pain, retroperitoneal hemorrhage.
Cardiovascular: Atrial fibrillation, atrial flutter, cerebral infarct, cerebral ischemia, congestive heart failure, heart arrest, hemorrhage, hypotension, myocardial infarction, myocardial ischemia, nodal arrhythmia, postural hypotension, supraventricular tachycardia, syncope, varicose vein, vasodilation, ventricular extrasystoles, ventricular tachycardia.
Digestive: Anorexia, cholelithiasis, colitis, duodenal ulcer, duodenitis, esophageal hemorrhage, esophagitis, increased GGT, gastritis, gastroenteritis, gum hemorrhage, hematemesis, melena, peptic ulcer, periodontal abscess, rectal hemorrhage, stomach ulcer, tongue edema.
Endocrine: Diabetes mellitus.
Hemic and Lymphatic: Anemia, ecchymosis, iron deficiency anemia, polycythemia, purpura.
Metabolic and Nutritional:: Increased creatinine, gout, hyperlipemia, hyperuricemia.
Musculoskeletal: Arthralgia, bone pain, bursitis.
Nervous: Anxiety, insomnia, neuralgia.
Respiratory: Asthma, epistaxis, hemoptysis, pneumonia, sinusitis.
Skin and Appendages: Dry skin, furunculosis, skin hypertrophy, urticaria.
Special Senses: Amblyopia, blindness, conjunctivitis, diplopia, ear pain, eye hemorrhage, retinal hemorrhage, tinnitus.
Urogenital: Albuminuria, cystitis, urinary frequency, vaginal hemorrhage, vaginitis

Post Marketing Experience

The following adverse events have been reported spontaneously from worldwide post-marketing experience since launch of cilostazol in the US.

- Blood and lymphatic system disorders:
  - agranulocytosis, aplastic anemia, granulocytopenia, thrombocytopenia, leukopenia, bleeding tendency
- Cardiac disorders:
  - Torsades de pointes, QTc prolongation (Torsades de pointes and QTc prolongation occurred in patients with cardiac disorders, e.g. complete atrioventricular block, cardiac failure and bradyarrythmia, when treated with cilostazol. Cilostazol was used “off label” due to its positive chronotropic action.)
- Gastrointestinal disorders:
  - gastrointestinal hemorrhage
- General disorders and administration site conditions:
  - pain, chest pain, hot flushes
- Hepatobiliary disorders:
  - hepatic dysfunction/abnormal liver function tests, jaundice
- Injury, poisoning and procedural complications:
  - extradural hematoma and subdural hematoma
- Investigations :
  - blood glucose increased, blood uric acid increased, platelet count decreased, white blood cell count decreased, increase in BUN (blood urea increased), blood pressure increase
- Nervous system disorders:
  - intracranial hemorrhage, cerebral hemorrhage, cerebrovascular accident
- Respiratory, thoracic and mediastinal disorders:
  - pulmonary hemorrhage, interstitial pneumonia
- Skin and subcutaneous tissue disorders:
  - hemorrhage subcutaneous, pruritus, skin eruptions including Stevens-Johnson syndrome, skin drug eruption (dermatitis medicamentosa)
- Vascular disorders:
  - subacute thrombosis (These cases of subacute thrombosis occurred in patients treated with aspirin and “off label” use of cilostazol for prevention of thrombotic complication after coronary stenting.)

OVERDOSAGE

Information on acute overdosage with cilostazol in humans is limited. The signs and symptoms of an acute overdose can be anticipated to be those of excessive pharmacologic effect: severe headache, diarrhea, hypotension, tachycardia, and possibly cardiac arrhythmias. The patient should be carefully observed and given supportive treatment. Since cilostazol is highly protein-bound, it is unlikely that it can be efficiently removed by hemodialysis or peritoneal dialysis. The oral LD50 of cilostazol is >5.0 g/kg in mice and rats and >2.0 g/kg in dogs.

DOSAGE AND ADMINISTRATION

The recommended dosage of cilostazol is 100 mg b.i.d. taken at least half an hour before or two hours after breakfast and dinner. A dose of 50 mg b.i.d. should be considered during coadministration of such inhibitors of CYP3A4 as ketoconazole, itraconazole, erythromycin and diltiazem, and during coadministration of such inhibitors of CYP2C19 as omeprazole.

Patients may respond as early as 2 to 4 weeks after the initiation of therapy, but treatment for up to 12 weeks may be needed before a beneficial effect is experienced.

Discontinuation of Therapy

The available data suggest that the dosage of cilostazol can be reduced or discontinued without rebound (i.e., platelet hyperaggregability).

HOW SUPPLIED

Cilostazol Tablets, USP 100mg are white,round compressed tablets debossed "cor" over "159" on one side and other side is plain.

They are supplied as follows:

Bottles of 30 | NDC 54868-5411-1
Bottles of 60 | NDC 54868-5411-0

STORAGE

Store at 20 to 25°C (68 to 77°F) excursions permitted to 15 to 30°C (59 to 86°F) [see USP Controlled Room Temperature].

Dispense in a tight container as defined in the USP/NF.

Keep this and all drugs out of the reach of children.

Rev. October 2009
MF # 334-04

Manufactured and Distributed by:
Corepharma LLC
Middlesex, NJ 08846

Relabeling and Repackaging by:
Physicians Total Care, Inc.
Tulsa, OK 74146

PATIENT INFORMATION ABOUT CILOSTAZOL (sil-OS-tah-zol) TABLETS, USP

Cilostazol Tablets 50 mg and 100 mg

Please read this leaflet before you start taking cilostazol and each time you renew it in case anything has changed. This leaflet does not replace careful discussions with your doctor. You and your doctor should discuss cilostazol when you start taking it and at regular check-ups. You should follow your doctor’s advice about when to have check-ups.

What is Cilostazol Tablets, USP for?

Cilostazol may improve the symptoms of patients with a medical condition called intermittent claudication.

What is intermittent claudication?

Intermittent claudication is pain in the legs that occurs with walking and disappears with rest. It occurs because narrowing or blockage of the arteries decreases blood flow to the legs. The decreased blood flow does not supply enough oxygen to the leg muscles during walking, resulting in these painful leg cramps.

What treatments are available for intermittent claudication?

The three main treatments available for intermittent claudication are:

- Exercise. Your doctor may advise an exercise program.
- Medication. Your doctor may prescribe a medication such as cilostazol. (See Who should not take cilostazol?)
- Surgery. Your doctor may recommend a surgical procedure to bypass the blocked segment of the artery. Another procedure is called a percutaneous transluminal angioplasty. In this procedure, a catheter (a flexible tube) is inserted into the artery to reduce the blockage and improve blood flow.

How does Cilostazol Tablets, USP work?

- The exact way that many drugs work is not well understood. Although how cilostazol works is not completely clear, its main effects are to dilate (widen) the arteries supplying blood to the legs and to decrease the ability of platelets in the blood to stick together. Platelets are particles that circulate in the blood and play a role in clotting
- Cilostazol may reduce the leg pain that patients with intermittent claudication experience, allowing them to walk farther before their leg pain occurs.
- Improvement in symptoms may occur as soon as 2 weeks, but could take up to 12 weeks. If you have not noticed any benefit from cilostazol after 12 weeks you and your doctor may wish to discuss other forms of treatment.
- Sometimes blood vessel disease of the legs causes pain at rest or breakdown of skin in the leg. Cilostazol has not been shown to work in patients with these problems.

Who should not take Cilostazol Tablets, USP?

- Patients who have congestive heart failure (CHF) must not take cilostazol.
  The most common symptoms of CHF are shortness of breath and swelling of the legs. However, other conditions may also cause these symptoms.
- Patients who have bleeding problems, such as a bleeding peptic ulcer, must not take cilostazol.
  Cilostazol decreases the ability of blood particles, called platelets, to stick together and this can increase the risk of bleeding.
  It is important that you discuss with your doctor whether you have CHF or bleeding problems.
- Over 1,300 patients took cilostazol in studies that lasted for 3 to 6 months. The mortality rate in these patients was similar to placebo (less than 1%). These studies were too small to be sure there is not some increased risk of dying with longer use or in patients sicker than those in the studies.

How should Cilostazol Tablets, USP be taken?

- Follow your doctor"s advice about how to take cilostazol.
- You should take cilostazol twice a day, at least one half-hour before or two hours after breakfast and dinner. Take cilostazol at about the same times each day.
- Do not share cilostazol with anyone else. It was prescribed only for you.
- Keep cilostazol and all drugs out of the reach of children.

Can Cilostazol Tablets, USP be taken with other drugs?

Certain drugs and foods can increase the amount of cilostazol in the blood. Because of this, your doctor may adjust your dose of cilostazol or even stop it if you are taking or are going to take one of the following medications.

Drugs Interacting With Cilostazol
Generic Name (Brand Name) | Type of Drug
erythromycin (such as E.E.S.®, Erythrocin®) | Antibiotic
ketoconazole (Nizoral®), itraconazole (Sporanox®) | Antifungal
diltiazem (Cardizem®) | Antihypertensive
omeprazole (Prilosec®) | Gastric acid reducer

This list does not include every drug that may interact with cilostazol. Therefore, you should tell your doctor about all medications that you are taking, including vitamins, herbal supplements and over-the-counter drugs you can buy without a prescription. You should also check with your doctor before taking a new medication after you have begun cilostazol.

What are the possible side effects of CIlostazol Tablets, USP?

Cilostazol may cause side effects including headache, diarrhea, abnormal stools, increased heart rate, and palpitations.

You should discuss possible side effects with your doctor before taking cilostazol and any time you think you are having a side effect.

Call your doctor for medical advice about side effects. You may report side effects to FDA at 1-800-FDA-1088.

This provides only a summary of information about cilostazol. If you have any questions about cilostazol, talk to your doctor.

Rev. October, 2009
MF # 334-04

Manufactured and Distributed by:
Corepharma LLC
Middlesex, NJ 08846

PACKAGE LABEL PRINCIPAL DISPLAY PANEL

Cilostazol Tablets, USP 100mg